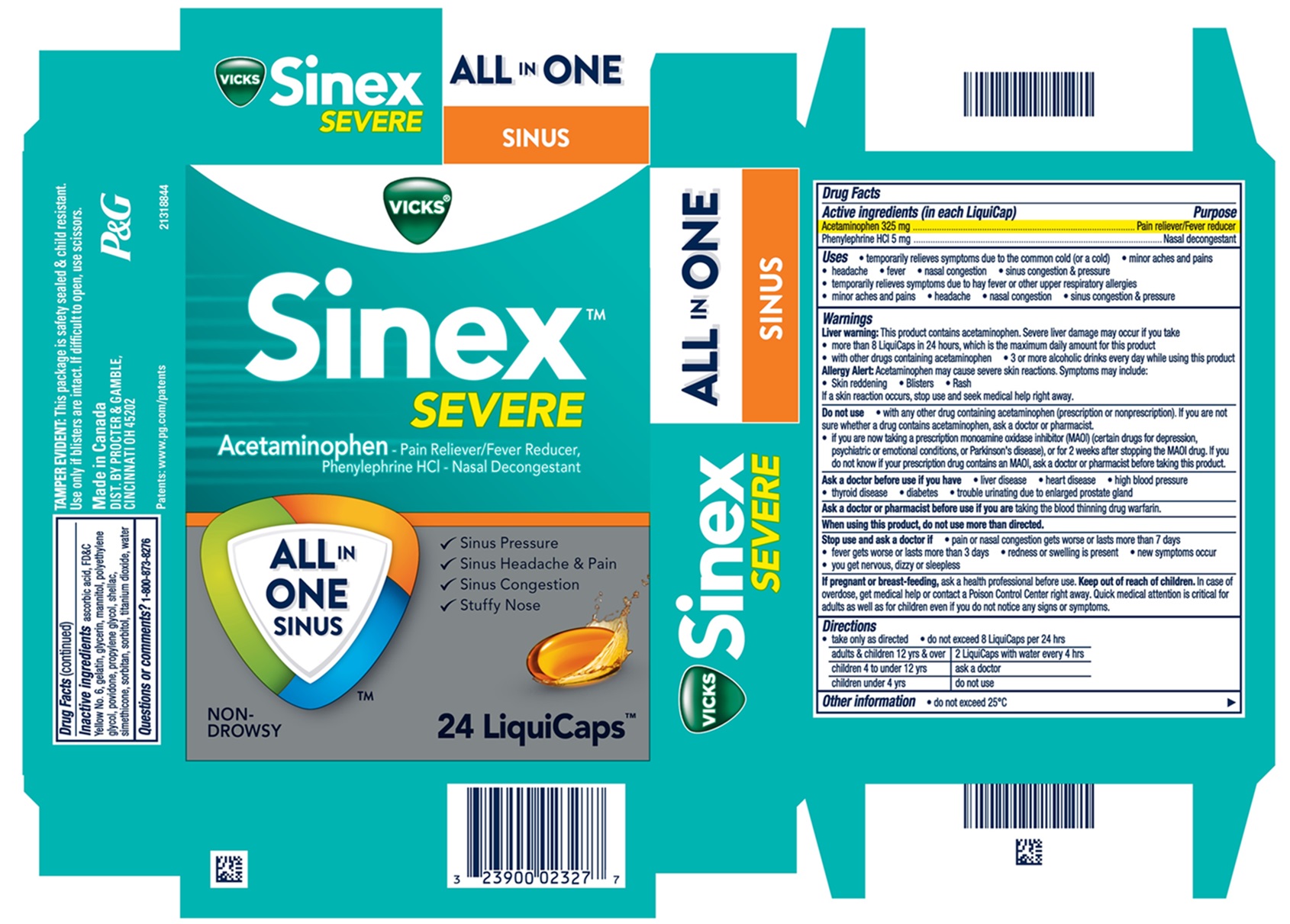 DRUG LABEL: Vicks Sinex Severe
NDC: 37000-950 | Form: CAPSULE, LIQUID FILLED
Manufacturer: The Procter & Gamble Manufacturing Company
Category: otc | Type: HUMAN OTC DRUG LABEL
Date: 20251120

ACTIVE INGREDIENTS: ACETAMINOPHEN 325 mg/1 1; PHENYLEPHRINE HYDROCHLORIDE 5 mg/1 1
INACTIVE INGREDIENTS: DIMETHICONE; SORBITAN; MANNITOL; SHELLAC; TITANIUM DIOXIDE; FD&C YELLOW NO. 6; GELATIN; GLYCERIN; POLYETHYLENE GLYCOL, UNSPECIFIED; PROPYLENE GLYCOL; WATER; SORBITOL; ASCORBIC ACID; POVIDONE

VICKS® Sinex ™ Severe ALL IN ONE™ SINUS
LiquiCaps

Drug Facts

Active ingredients (in each LiquiCap)

Acetaminophen 325 mg

Phenylephrine HCl 5 mg

Purpose

Pain reliever/fever reducer

Nasal decongestant

Uses

temporarily relieves symptoms due to the common cold (or a cold)

- minor aches and pains
- headache
- fever
- nasal congestion
- sinus congestion & pressure
- temporarily relieves symptoms due to hay fever or other upper respiratory allergies
- minor aches and pains
- headache
- nasal congestion
- sinus congestion & pressure

Warnings

Liver warning

This product contains acetaminophen. Severe liver damage may occur if you take

- more than 8 LiquiCaps in 24 hours, which is the maximum daily amount for this product
- with other drugs containing acetaminophen
- 3 or more alcoholic drinks daily while using this product

Allergy Alert:

acetaminophen may cause severe skin reactions. Symptoms may include:

- Skin reddening
- Blisters
- Rash

If a skin reaction occurs, stop use and seek medical help right away

Do not use

- with any other drug containing acetaminophen (prescription or nonprescription). If you are not sure whether a drug contains acetaminophen, ask a doctor or pharmacist.
- if you are now taking a prescription monoamine oxidase inhibitor (MAOI) (certain drugs for depression, psychiatric or emotional conditions, or Parkinson's disease), or for 2 weeks after stopping the MAOI drug. If you do not know if your prescription drug contains an MAOI, ask a doctor or pharmacist before taking this product.

Ask a doctor before use if you have

- liver disease
- heart disease
- high blood pressure
- thyroid disease
- diabetes
- trouble urinating due to enlarged prostate gland

Ask a doctor or pharmacist before use if you are

taking the blood thinning drug warfarin

When using this product,

do not use more than directed

Stop use and ask a doctor if

- pain, nasal congestion, or cough gets worse or lasts more than 7 days
- fever gets worse or lasts more than 3 days
- redness or swelling is present
- new symptoms occur
- you get nervous, dizzy or sleepless

If pregnant or breast-feeding,

ask a health professional before use.

Keep out of reach of children.

OVERDOSAGE

In case of overdose, get medical help or contact a Poison Control Center right away. Quick medical attention is critical for adults as well as for children even if you do not notice any signs or symptoms.

Directions

- take only as directed
- do not exceed 8 LiquiCaps per 24 hrs

adults & children 12 yrs & over | 2 LiquiCaps with water every 4 hrs
children 4 to under 12 yrs | ask a doctor
children under 4 yrs | do not use

Other information

- do not exceed 25ºC

Inactive ingredients

ascorbic acid, FD&C Yellow No. 6, gelatin, glycerin, mannitol, polyethylene glycol, povidone, propylene glycol, shellac, simethicone, sorbitan, sorbitol, titanium dioxide, water

Questions?

1-800-873-8276

TAMPER EVIDENT: This package is safety sealed & child resistant. Use only if blisters are intact. If difficult to open, use scissors.

Made in Canada

DIST. BY PROCTER & GAMBLE,
CINCINNATI OH 45202

PRINCIPAL DISPLAY PANEL - 24 LiquiCap Carton

VICKS®

Sinex ™

SEVERE

Acetaminophen - Pain Reliever/Fever Reducer,

Phenylephrine HCl - Nasal Decongestant

ALL IN ONE SINUS™

- Sinus Pressure
- Sinus Headache & Pain

- Sinus Congestion
- Stuffy Nose

NON-DROWSY

24 LiquiCaps ™